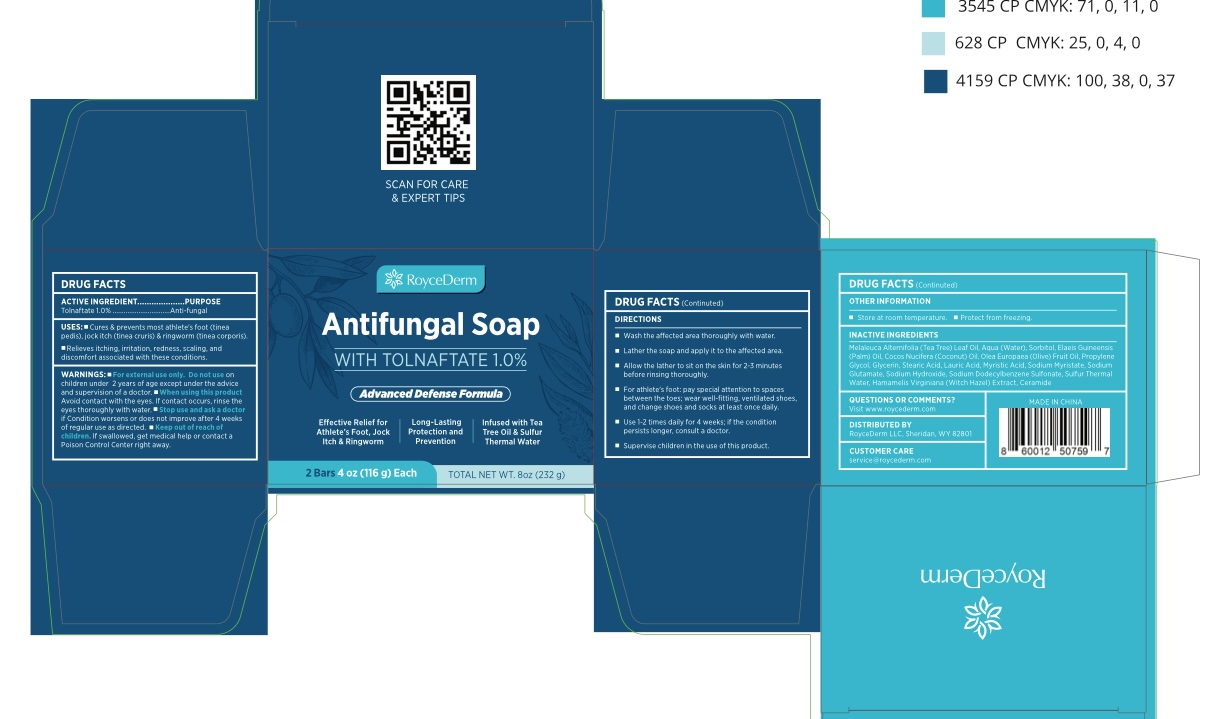 DRUG LABEL: Antifungal Medicated Bar
NDC: 85261-001 | Form: SOAP
Manufacturer: Haikou Pucao Trading Co.,Ltd
Category: otc | Type: HUMAN OTC DRUG LABEL
Date: 20250325

ACTIVE INGREDIENTS: TOLNAFTATE 10 mg/1 g
INACTIVE INGREDIENTS: MELALEUCA ALTERNIFOLIA (TEA TREE) LEAF OIL; OLEA EUROPAEA (OLIVE) FRUIT OIL; WATER; CERAMIDE NP; SULFUR; SORBITOL; LAURIC ACID; ELAEIS GUINEENSIS (PALM) OIL; PROPYLENE GLYCOL; SODIUM HYDROXIDE; GLYCERIN; SODIUM DODECYLBENZENESULFONATE; SODIUM MYRISTATE; SODIUM GLUTAMATE; COCOS NUCIFERA (COCONUT) OIL; STEARIC ACID; MYRISTIC ACID; HAMAMELIS VIRGINIANA (WITCH HAZEL) LEAF WATER

RoyceDerm antifungal soap

ACTIVE INGREDIENT

Tolnaftate 1%

PURPOSE

anti-fungal

INDICATIONS AND USAGE

Cures & prevents most athlete's foot(tinea pedis), jock itch(tinea cruris) & ringworm (tinea corporis).
Relieves itching, irritation, redness, scaling, and discomfort associated with these conditions.

WARNINGS

Forx external use only

DO NOT USE

on children under 2 years of age except under the advice and supervision of a doctor.

WHEN USING

avoid contact with the eyes. If contact occurs, rinse the eyes thoroughly with water.

STOP USE

if condition worsens or does not improve after 4 weeks of regular use as directed.

KEEP OUT OF REACH OF CHILDREN

If swallowed, get medical help or contact a Poison Control Center right away.

DOSAGE AND ADMINISTRATION

Wash the affected area thoroughly with water.
Lather the soap and apply it to the affected area.
Allow the lather to sit on the skin for 2-3 minutes before rinsing thoroughly.
For athlete's foot: pay special attention to spaces between the toes; wear well-fitting, ventilated shoes, and change shoes and socks at least once daily.
Use 1-2 times daily for 4 weeks; if the condition persists longer, consult a doctor.
Supervise children in the use of this product.

OTHER SAFETY INFORMATION

Store at room temperature.
Protect from freezing.

INACTIVE INGREDIENT

Melaleuca Alternifolia (Tea Tree) Leaf Oil, Aqua (Water), Sorbitol, Elaeis Guineensis (Palm) Oil, Cocos Nucifera (Coconut) Oil, Olea Europaea (Olive) Fruit Oil, Propylene Glycol, Glycerin, Stearic Acid, Lauric Acid, Myristic Acid, Sodium Myristate, Sodium Glutamate, Sodium Hydroxide, Sodium Dodecylbenzene Sulfonate, Sulfur, Hamamelis Virginiana (Witch Hazel) Extract, Ceramide NP.

QUESTIONS

Visit at www.roycederm.com